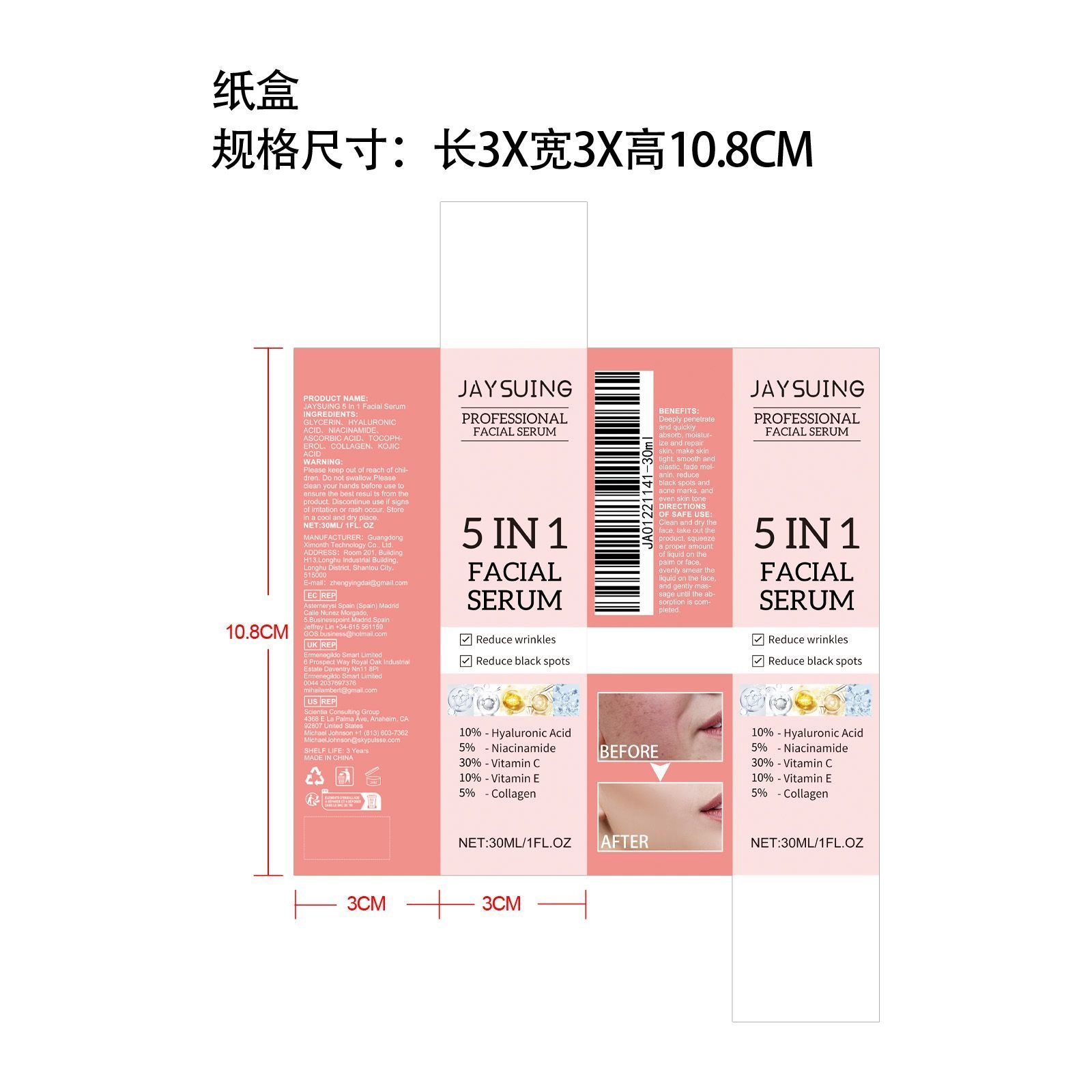 DRUG LABEL: JAYSUING 5 In 1 Facial Serum
NDC: 84660-029 | Form: LIQUID
Manufacturer: Guangdong Ximonth Technology Co., Ltd.
Category: otc | Type: HUMAN OTC DRUG LABEL
Date: 20240926

ACTIVE INGREDIENTS: KOJIC ACID 3 mg/30 mg; NIACINAMIDE 1.5 mg/30 mg; MARINE COLLAGEN, SOLUBLE 1.5 mg/30 mg; ASCORBIC ACID 4.5 mg/30 mg
INACTIVE INGREDIENTS: HYALURONIC ACID 6 mg/30 mg; GLYCERIN 9 mg/30 mg; TOCOPHEROL 4.5 mg/30 mg

Active Ingredient(s)

HYALURONIC ACID、NIACINAMIDE、ASCORBIC ACID、TOCOPHEROL、COLLAGEN、KOJIC ACID

INACTIVE INGREDIENT

GLYCERIN

Purpose

Make skin tight, smooth andelastic, fade melanin,

Do not use

Discontinue use if signs of irritation or rash occur.

STOP USE

Discontinue use if signs of irritation or rash occur.

KEEP OUT OF REACH OF CHILDREN

Please keep out of reach of children. Do not swallow.

Warnings

Please keep out of reach of children.Do not swallow.Please clean your hands before use to ensure the best results from the product.Discontinue use if signs of irritation or rash occur.Store in a cool and dry place.

STORAGE AND HANDLING

Avoid freezing and excessive heat above 40C (104F) ）
Store in a cool and dry place.

Use

Clean and dry the face, take out the product, squeeze a proper amount of liquid on the palm or face, evenly smear the liquid on the face, and gently massage until the absorption is completed.